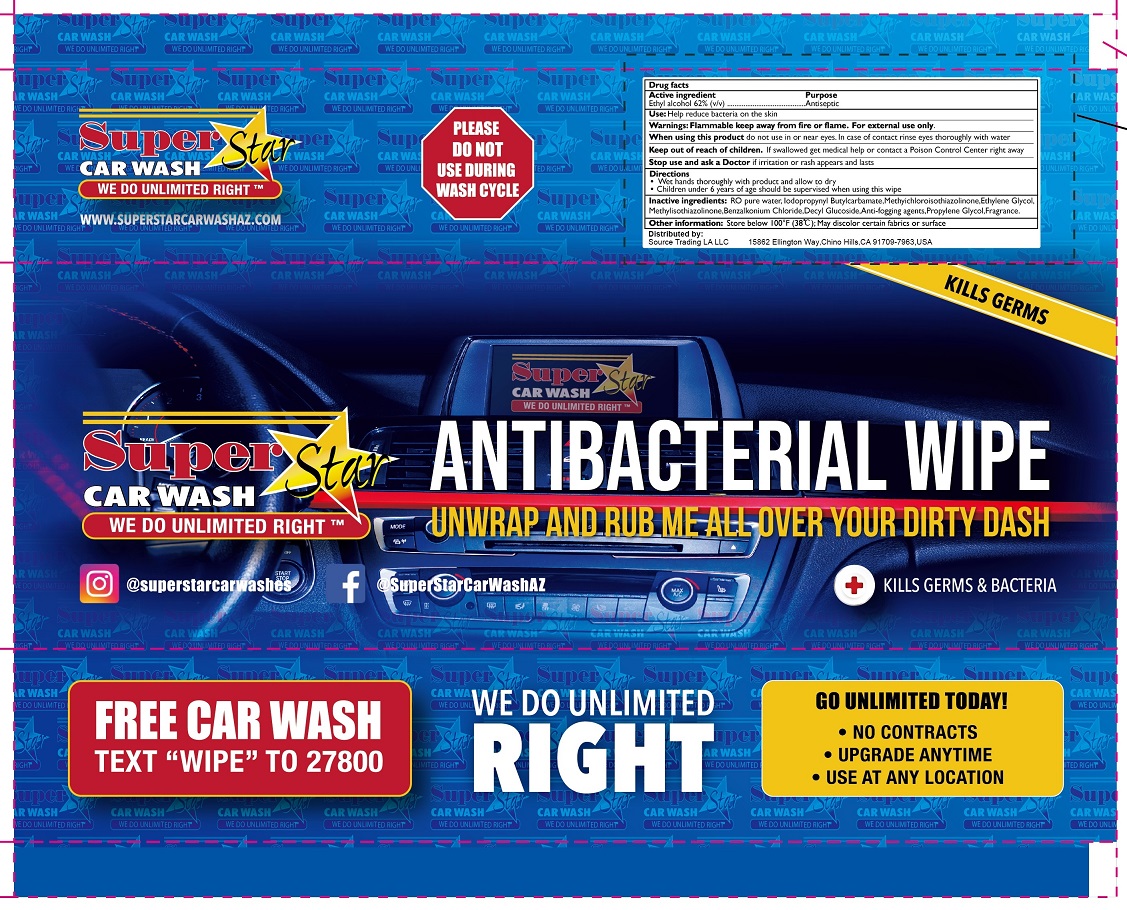 DRUG LABEL: Wet Wipes
NDC: 77435-022 | Form: CLOTH
Manufacturer: HAINING LILY CLEANING PRODUCTS CO., LTD
Category: otc | Type: HUMAN OTC DRUG LABEL
Date: 20210117

ACTIVE INGREDIENTS: ALCOHOL 62 g/100 g
INACTIVE INGREDIENTS: WATER; ETHYLENE GLYCOL; METHYLISOTHIAZOLINONE; BENZALKONIUM CHLORIDE; DECYL GLUCOSIDE; PROPYLENE GLYCOL

Wipes

Active Ingredient

Ethyl Alcohol 62%

Purpose

Antiseptic

USE

Help reduce bacteria on the skin.

Warning

- Flammable, keep away from fire or flame. For external use only.
- When using this product, Do not use in or near the eyes. In case of contact, rinse eyes thoroughly with water.

- Stop use and ask a doctor, if irritaion or rash appears and lasts.

Other Information：

- Store below 100℉ (38 ℃)
- May discolor some fabrics or surface

KEEP OUT OF REACH OF CHILDREN

●If swallowed, get medical help or contact a Poison Contrl Center right away.

Directions

- Wet hands thoroughluy with produt and allow to dry.
- Children under 6 years of age should be supervised when using this wipe.

Inactive ingredients

RIO Pure Water, lodopropynyl Butylcarbamate, methyichloroisothiazolinone, Ethylene glycol, Methylisothiazolinone, Benzalkonium Chloride, Decyl Glucoside, Anti-fogging agents, Propylene Glycol, Fragrance.